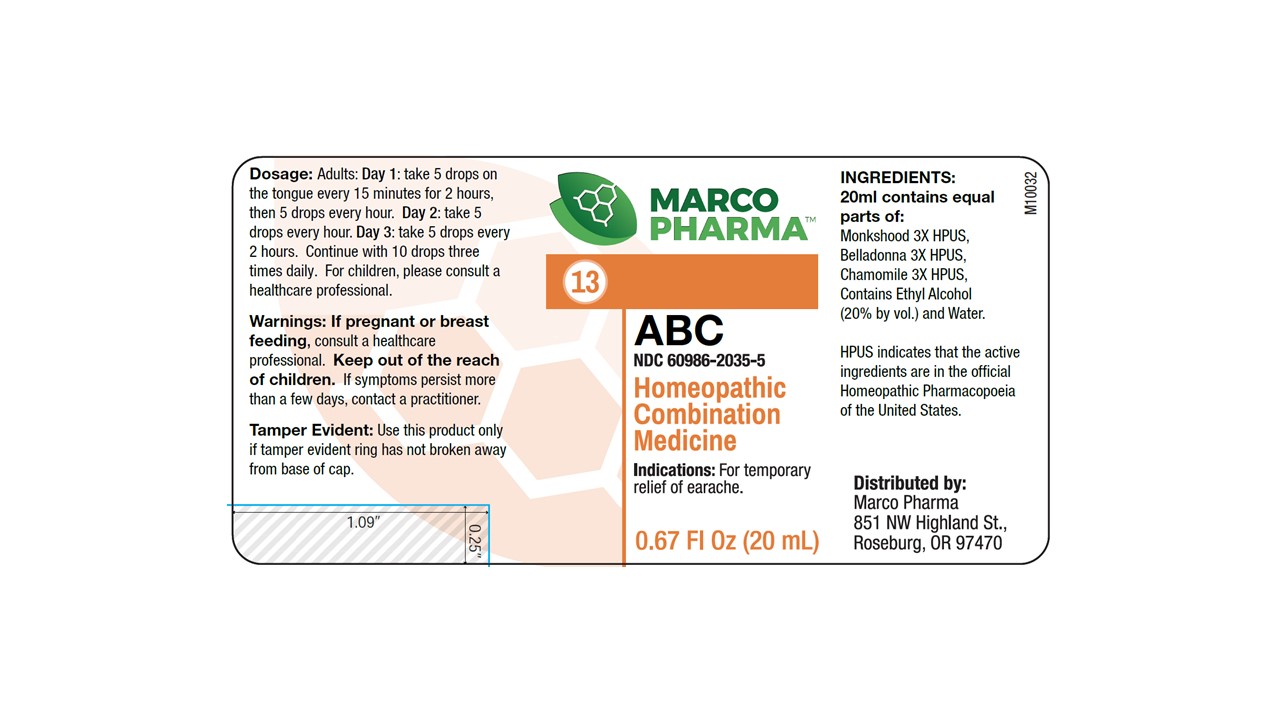 DRUG LABEL: ABC
NDC: 60986-2035 | Form: LIQUID
Manufacturer: MARCO PHARMA INTERNATIONAL LLC
Category: homeopathic | Type: HUMAN OTC DRUG LABEL
Date: 20260112

ACTIVE INGREDIENTS: ACONITUM NAPELLUS 3 [hp_X]/100 mL; MATRICARIA RECUTITA 3 [hp_X]/100 mL; BELLADONNA LEAF 3 [hp_X]/100 mL
INACTIVE INGREDIENTS: ALCOHOL; WATER

ABC

ACTIVE INGREDIENTS

ACONITUM NAPELLUS 3X HPUS

CHAMOMILLA 3X HPUS

BELLADONA 3X HPUS

INACTIVE INGREDIENT

ETHYL ALCOHOL (20% BY VOL) AND WATER

PURPOSE

FOR TEMPORARY RELIEF OF COLD AND FLU SYMPTOMS WITH TEMPERATURE

WARNINGS

KEEP OUT OF REACH OF CHILDREN

WARNINGS

IF PREGNANT OR BREAST-FEEDING, CONSULT A HEALTH PROFESSIONAL BEFORE USE

WARNINGS

IF SYMPTOMS PERSIST MORE THAN A FEW DAYS, CONTACT LICENSED PRACTIONER.

INDICATIONS AND USAGE

FOR TEMPORARY RELIEF OF EARACHE

DOSAGE AND ADMINISTRATION

ADULTS AND CHILDREN: DAY 1; TAKE 5 DROPS ON THE TONGUE EVERY 15 MINUTES FOR 2 HOURS. THEN TAKE 5 DROPS ONCE EVERY HOUR. DAY 2; TAKE 5 DROPS ONCE EVERY HOUR. DAY 3; TAKE 5 DROPS EVERY TWO HOURS. CONTINUE WITH 10 DROPS THREE TIMES DAILY